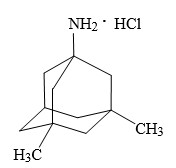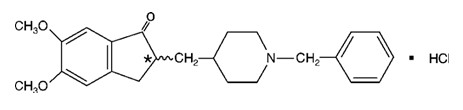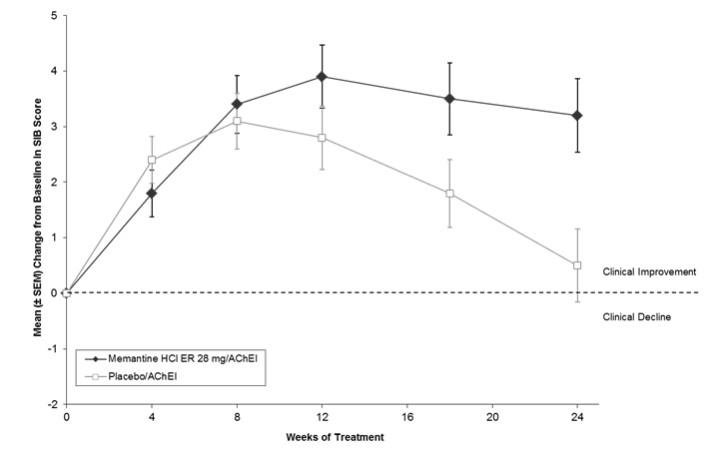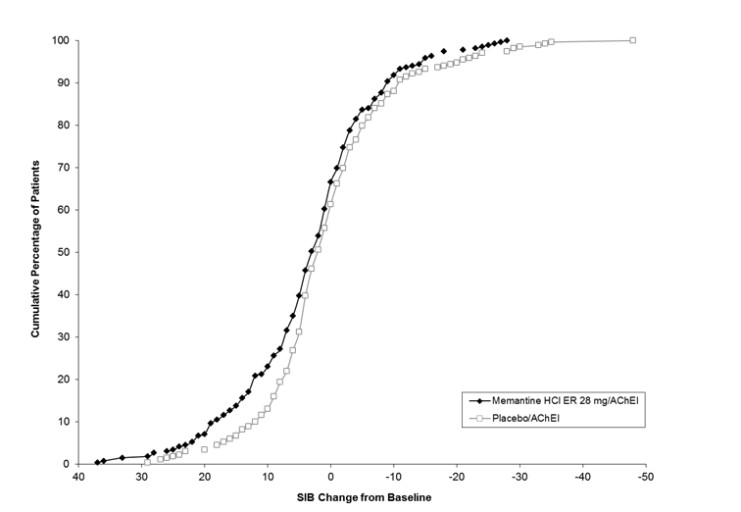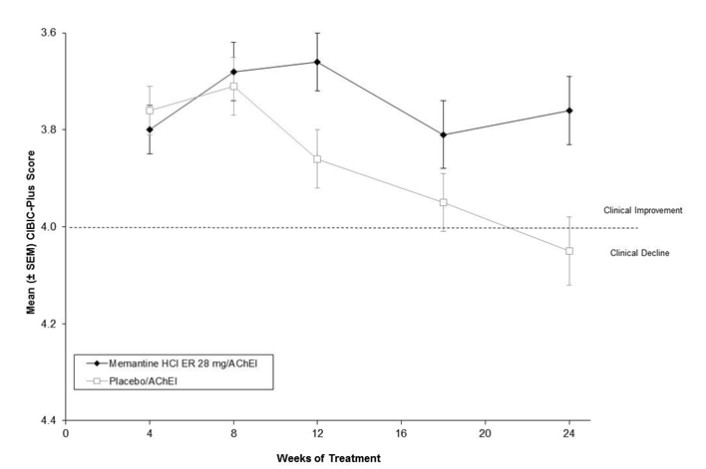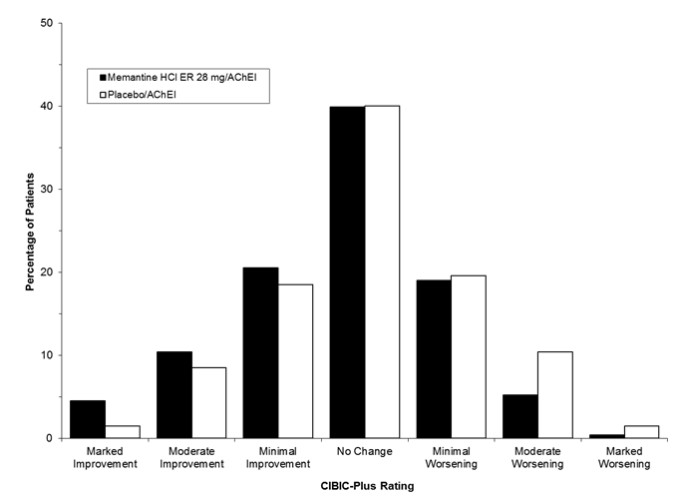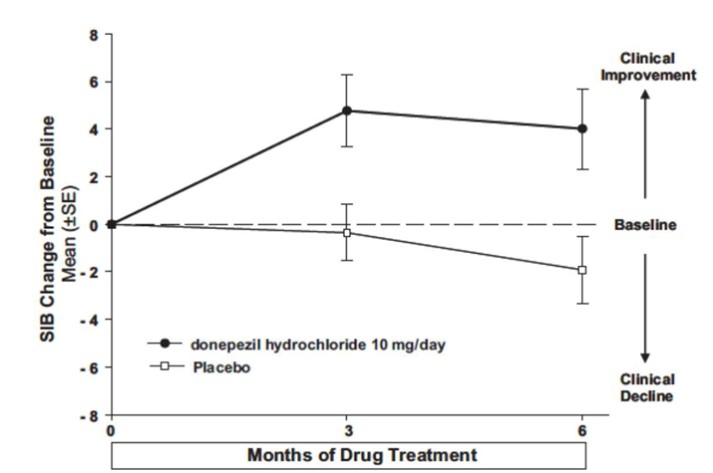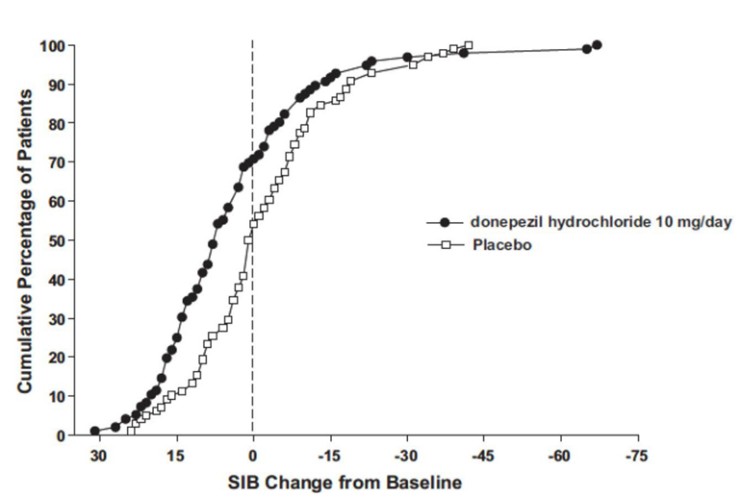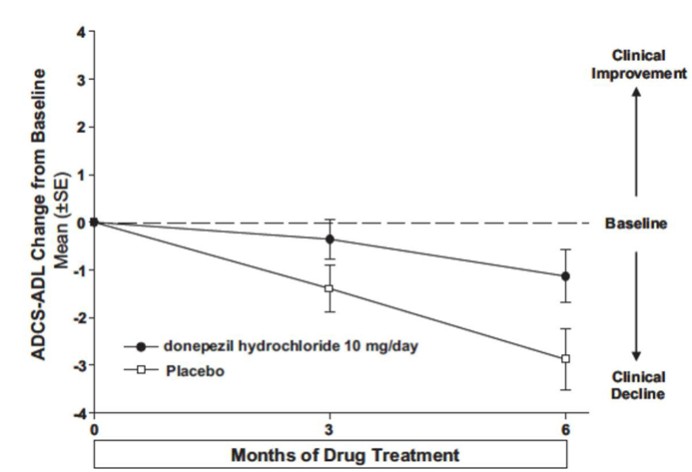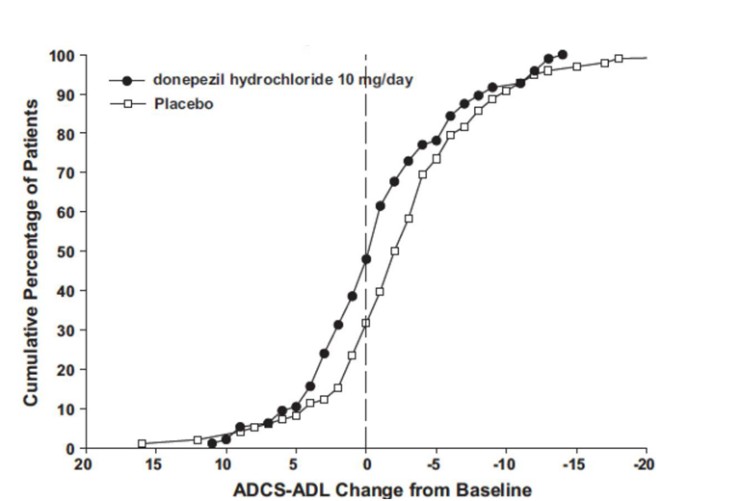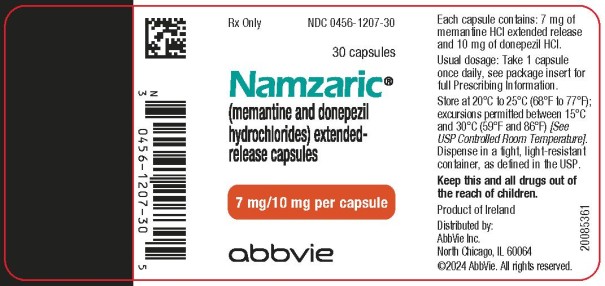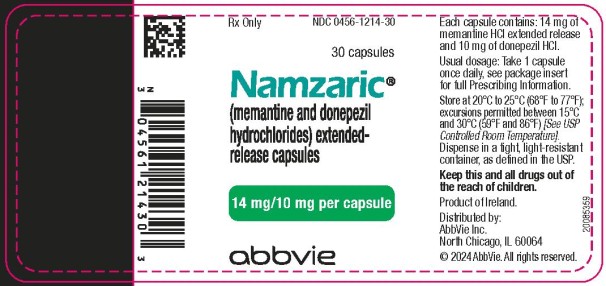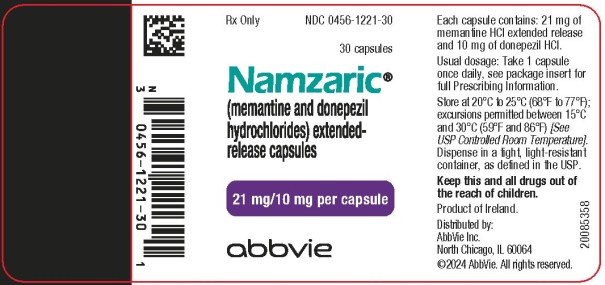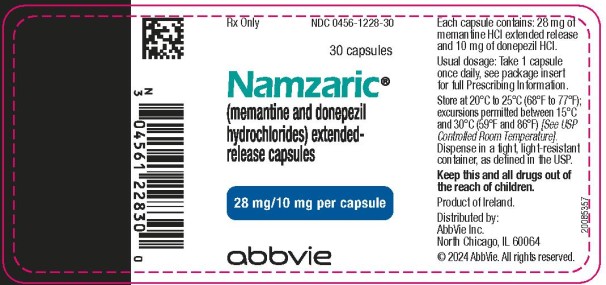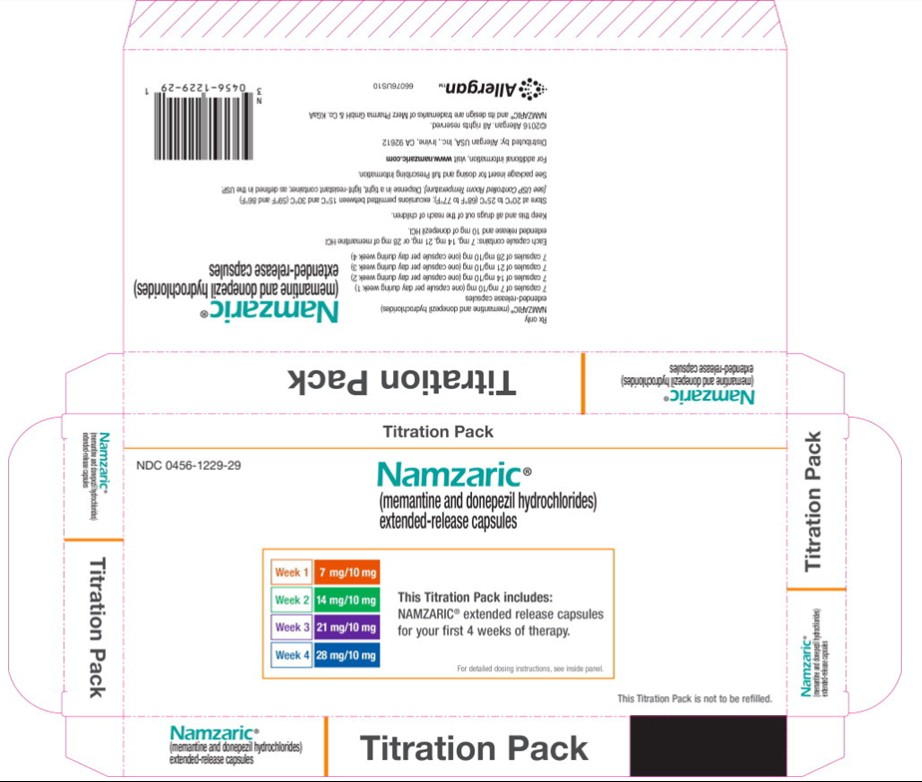 DRUG LABEL: Namzaric
NDC: 0456-1214 | Form: CAPSULE
Manufacturer: Allergan, Inc.
Category: prescription | Type: HUMAN PRESCRIPTION DRUG LABEL
Date: 20240513

ACTIVE INGREDIENTS: memantine hydrochloride 14 mg/1 1; donepezil hydrochloride 10 mg/1 1
INACTIVE INGREDIENTS: SUCROSE; POVIDONE, UNSPECIFIED; TALC; HYPROMELLOSE, UNSPECIFIED; POLYETHYLENE GLYCOL, UNSPECIFIED; ETHYLCELLULOSE, UNSPECIFIED; OLEIC ACID; MEDIUM-CHAIN TRIGLYCERIDES; LACTOSE MONOHYDRATE; CELLULOSE, MICROCRYSTALLINE; STARCH, CORN; SILICON DIOXIDE; MAGNESIUM STEARATE; TITANIUM DIOXIDE; GELATIN, UNSPECIFIED; SHELLAC; FERROSOFERRIC OXIDE; FD&C BLUE NO. 1; FERRIC OXIDE YELLOW

HIGHLIGHTS OF PRESCRIBING INFORMATION

These highlights do not include all the information needed to use NAMZARIC capsules safely and effectively. See full prescribing information for NAMZARIC capsules.
NAMZARIC (memantine and donepezil hydrochlorides) extended-release capsules, for oral use
Initial U.S. Approval: 2014

1 INDICATIONS AND USAGE

NAMZARIC is a combination of memantine hydrochloride, an NMDA receptor antagonist, and donepezil hydrochloride, an acetylcholinesterase inhibitor, indicated for the treatment of moderate to severe dementia of the Alzheimer’s type in patients stabilized on 10 mg of donepezil hydrochloride once daily. (1)

2 DOSAGE AND ADMINISTRATION

- For patients on donepezil hydrochloride 10 mg only, the recommended starting dose of NAMZARIC is 7 mg/10 mg, taken once daily in the evening. The dose should be increased in 7 mg increments to the recommended maintenance dose of 28 mg/10 mg. The minimum recommended interval between dose increases is one week. (2.1)
- Patients on memantine hydrochloride (10 mg twice daily or 28 mg extended-release once daily) and donepezil hydrochloride 10 mg once daily can be switched to NAMZARIC 28 mg/10 mg, taken once daily in the evening. (2.1)
- NAMZARIC can be taken with or without food, whole or sprinkled on applesauce; do not divide, chew, or crush. (2.2)
- Severe renal impairment: the recommended maintenance dose for NAMZARIC is 14 mg/10 mg once daily in the evening. (2.3)

3 DOSAGE FORMS AND STRENGTHS

Extended-Release Capsules:

- 7 mg memantine hydrochloride and 10 mg donepezil hydrochloride (3)
- 14 mg memantine hydrochloride and 10 mg donepezil hydrochloride (3)
- 21 mg memantine hydrochloride and 10 mg donepezil hydrochloride (3)
- 28 mg memantine hydrochloride and 10 mg donepezil hydrochloride (3)

4 CONTRAINDICATIONS

NAMZARIC is contraindicated in patients with known hypersensitivity to memantine hydrochloride, donepezil hydrochloride, piperidine derivatives, or to any excipients used in the formulation. (4)

5 WARNINGS AND PRECAUTIONS

- NAMZARIC is likely to exaggerate succinylcholine-type muscle relaxation during anesthesia. (5.1)
- NAMZARIC may have vagotonic effects on the sinoatrial and atrioventricular nodes manifesting as bradycardia or heart block. (5.2)
- Monitor patients for symptoms of active or occult gastrointestinal bleeding, especially those at increased risk for developing ulcers. (5.3)
- NAMZARIC can cause diarrhea, nausea, and vomiting. (5.4)
- NAMZARIC may cause bladder outflow obstructions. (5.5)
- Conditions that raise urine pH may decrease the urinary elimination of memantine, resulting in increased plasma levels of memantine. (5.5, 7.1)

6 ADVERSE REACTIONS

- The most common adverse reactions, occurring at a frequency of at least 5% and greater than placebo with memantine hydrochloride extended-release 28 mg/day, were headache, diarrhea, and dizziness. (6.1)
- The most common adverse reactions, occurring at a frequency of at least 5% in patients receiving donepezil hydrochloride and at twice or more the placebo rate, include diarrhea, anorexia, vomiting, nausea, and ecchymosis. (6.1)

To report SUSPECTED ADVERSE REACTIONS, contact AbbVie Inc. at 1-800-678-1605 or FDA at 1-800-FDA-1088 or www.fda.gov/medwatch.

7 DRUG INTERACTIONS

- Combined use with NMDA antagonists: use with caution. (7.2)
- NAMZARIC may interfere with anticholinergic medications. (7.4)
- Concomitant administration of succinylcholine, similar neuromuscular blocking agents, or cholinergic agonists may lead to synergistic effect. (7.5)

FULL PRESCRIBING INFORMATION

1 INDICATIONS AND USAGE

NAMZARIC is indicated for the treatment of moderate to severe dementia of the Alzheimer’s type in patients stabilized on 10 mg of donepezil hydrochloride once daily.

2 DOSAGE AND ADMINISTRATION

2.1 Recommended Dosing

The recommended dose of NAMZARIC is 28 mg/10 mg once daily.

For patients stabilized on donepezil and not currently on memantine:

For patients stabilized on donepezil hydrochloride 10 mg and not currently on memantine hydrochloride, the recommended starting dose of NAMZARIC is 7 mg/10 mg, taken once a day in the evening. The dose should be increased in 7 mg increments of the memantine hydrochloride component to the recommended maintenance dose of 28 mg/10 mg once daily. The minimum recommended interval between dose increases is one week. The dose should only be increased if the previous dose has been well tolerated. The maximum dose is 28 mg/10 mg once daily.

For patients stabilized on both donepezil and memantine:

Patients stabilized on memantine hydrochloride (10 mg twice daily or 28 mg extended-release once daily) and donepezil hydrochloride 10 mg once daily can be switched to NAMZARIC 28 mg/10 mg, taken once a day in the evening. Patients should start NAMZARIC the day following the last dose of memantine hydrochloride and donepezil hydrochloride administered separately.

If a patient misses a single dose of NAMZARIC, the next dose should be taken as scheduled, without doubling up the dose.

2.2 Administration Information

NAMZARIC can be taken with or without food. NAMZARIC capsules can be taken intact or may be opened, sprinkled on applesauce, and swallowed without chewing. The entire contents of each NAMZARIC capsule should be consumed; the dose should not be divided.

Except when opened and sprinkled on applesauce, as described above, NAMZARIC capsules should be swallowed whole. NAMZARIC capsules should not be divided, chewed, or crushed.

2.3 Dosing in Patients with Severe Renal Impairment

For patients stabilized on donepezil and not currently on memantine:

For patients with severe renal impairment (creatinine clearance 5-29 mL/min, based on the Cockcroft-Gault equation) stabilized on donepezil hydrochloride 10 mg once daily and not currently on memantine hydrochloride, the recommended starting dose of NAMZARIC is 7 mg/10 mg taken once a day in the evening. The dose should be increased to the recommended maintenance dose of 14 mg/10 mg once daily in the evening after a minimum of one week [see Use in Specific Populations (8.6)].

For patients stabilized on both donepezil and memantine:

Patients with severe renal impairment, stabilized on memantine hydrochloride (5 mg twice daily or 14 mg extended-release once daily) and donepezil hydrochloride 10 mg once daily, can be switched to NAMZARIC 14 mg/10 mg, taken once daily in the evening.

3 DOSAGE FORMS AND STRENGTHS

Extended-Release Capsules:

- 7 mg memantine hydrochloride and 10 mg donepezil hydrochloride: light green opaque body and an orange opaque cap with a black “FL 7/10” radial imprint
- 14 mg memantine hydrochloride and 10 mg donepezil hydrochloride: light green opaque capsules with a black “FL 14/10” radial imprint
- 21 mg memantine hydrochloride and 10 mg donepezil hydrochloride: white opaque body and an orange opaque cap with a black “FL 21/10” radial imprint
- 28 mg memantine hydrochloride and 10 mg donepezil hydrochloride: blue opaque capsules with a black “FL 28/10” radial imprint

4 CONTRAINDICATIONS

NAMZARIC is contraindicated in patients with known hypersensitivity to memantine hydrochloride, donepezil hydrochloride, piperidine derivatives, or to any excipients used in the formulation.

5 WARNINGS AND PRECAUTIONS

5.1 Anesthesia

Donepezil hydrochloride, an active ingredient in NAMZARIC, as a cholinesterase inhibitor, is likely to exaggerate succinylcholine-type muscle relaxation during anesthesia.

5.2 Cardiovascular Conditions

Because of their pharmacological action, cholinesterase inhibitors may have vagotonic effects on the sinoatrial and atrioventricular nodes. This effect may manifest as bradycardia or heart block in patients both with and without known underlying cardiac conduction abnormalities. Syncopal episodes have been reported in association with the use of donepezil hydrochloride, an active ingredient in NAMZARIC.

5.3 Peptic Ulcer Disease and Gastrointestinal Bleeding

Through their primary action, cholinesterase inhibitors may be expected to increase gastric acid secretion due to increased cholinergic activity. Clinical studies of donepezil hydrochloride in a dose of 5 mg/day to 10 mg/day have shown no increase, relative to placebo, in the incidence of either peptic ulcer disease or gastrointestinal bleeding. Patients treated with NAMZARIC should be monitored closely for symptoms of active or occult gastrointestinal bleeding, especially those at increased risk for developing ulcers, e.g., those with a history of ulcer disease or those receiving concurrent nonsteroidal anti-inflammatory drugs (NSAIDs).

5.4 Nausea and Vomiting

Donepezil hydrochloride, an active ingredient in NAMZARIC, when initiated, as a predictable consequence of its pharmacological properties, has been shown to produce diarrhea, nausea, and vomiting. Although in most cases, these effects have been mild and transient, sometimes lasting one to three weeks, and have resolved during continued use of donepezil hydrochloride, patients should be observed closely at the initiation of treatment.

5.5 Genitourinary Conditions

Although not observed in clinical trials of donepezil hydrochloride, an active ingredient in NAMZARIC, cholinomimetics may cause bladder outflow obstruction.

Conditions that raise urine pH may decrease the urinary elimination of memantine, an active ingredient in NAMZARIC, resulting in increased plasma levels of memantine [see Drug Interactions (7.1)].

5.6 Seizures

Cholinomimetics, including donepezil hydrochloride, an active ingredient in NAMZARIC, are believed to have some potential to cause generalized convulsions. However, seizure activity also may be a manifestation of Alzheimer’s disease.

5.7 Pulmonary Conditions

Because of their cholinomimetic actions, cholinesterase inhibitors should be prescribed with care to patients with a history of asthma or obstructive pulmonary disease.

6 ADVERSE REACTIONS

The following serious adverse reactions are discussed below and elsewhere in the labeling.

- Cardiovascular Conditions [see Warnings and Precautions (5.2)]
- Peptic Ulcer Disease and Gastrointestinal Bleeding [see Warnings and Precautions (5.3)]
- Nausea and Vomiting [see Warnings and Precautions (5.4)]
- Genitourinary Conditions [see Warnings and Precautions (5.5)]
- Seizures [see Warnings and Precautions (5.6)]
- Pulmonary Conditions [see Warnings and Precautions (5.7)]

6.1 Clinical Trials Experience

Because clinical trials are conducted under widely varying conditions, adverse reaction rates observed in the clinical trials of a drug cannot be directly compared to rates in the clinical trials of another drug and may not reflect the rates observed in practice.

Memantine Hydrochloride

Memantine hydrochloride extended-release was evaluated in a double-blind, placebo-controlled trial in 676 patients with moderate to severe dementia of the Alzheimer’s type (341 patients treated with memantine 28 mg/day dose and 335 patients treated with placebo) for a treatment period up to 24 weeks. Of the patients randomized, 236 treated with memantine 28 mg/day and 227 treated with placebo were on a stable dose of donepezil for 3 months prior to screening.

Adverse Reactions Leading to Discontinuation with Memantine Hydrochloride

In the placebo-controlled clinical trial of memantine hydrochloride extended-release, the proportion of patients in the memantine hydrochloride extended-release 28 mg/day dose group and in the placebo group who discontinued treatment due to adverse reactions was 10% and 6%, respectively. The most common adverse reaction in the memantine hydrochloride extended- release treated group that led to treatment discontinuation was dizziness, at a rate of 1.5%.

Most Common Adverse Reactions with Memantine Hydrochloride

The most common adverse reactions with memantine hydrochloride extended-release in patients with moderate to severe Alzheimer’s disease, defined as those occurring at a frequency of at least 5% in the memantine hydrochloride extended-release group and at a higher frequency than placebo, were headache, diarrhea, and dizziness.

Table 1 lists adverse reactions that occurred at an incidence of ≥ 2% in the memantine hydrochloride extended-release treated group and occurred at a rate greater than placebo.

Table 1: Adverse reactions with memantine hydrochloride extended-release in patients with moderate to severe Alzheimer’s disease
Adverse Reaction | Placebo (n = 335) % | Memantine hydrochloride extended-release 28 mg (n = 341) %
Gastrointestinal Disorders
Diarrhea | 4 | 5
Constipation | 1 | 3
Abdominal pain | 1 | 2
Vomiting | 1 | 2
Infections and Infestations
Influenza | 3 | 4
Investigations
Increased weight | 1 | 3
Musculoskeletal and Connective Tissue Disorders
Back pain | 1 | 3
Nervous System Disorders
Headache | 5 | 6
Dizziness | 1 | 5
Somnolence | 1 | 3
Psychiatric Disorders
Anxiety | 3 | 4
Depression | 1 | 3
Aggression | 1 | 2
Renal and Urinary Disorders
Urinary incontinence | 1 | 2
Vascular Disorders
Hypertension | 2 | 4
Hypotension | 1 | 2

Donepezil hydrochloride

Adverse Reactions Leading to Discontinuation with Donepezil Hydrochloride

In controlled clinical trials of donepezil hydrochloride, the rate of discontinuation due to adverse reactions for patients treated with donepezil hydrochloride was approximately 12%, compared to 7% for patients treated with placebo. The most common adverse reactions leading to discontinuation, defined as those occurring in at least 2% of donepezil hydrochloride patients and at twice or more the incidence seen with placebo, were anorexia (2%), nausea (2%), diarrhea (2%) and urinary tract infection (2%).

Most Common Adverse Reactions with Donepezil Hydrochloride

The most common adverse reactions reported with donepezil hydrochloride in controlled clinical trials in patients with severe Alzheimer’s disease, defined as those occurring at a frequency of at least 5% in the donepezil hydrochloride group and at twice or more the placebo rate, were diarrhea, anorexia, vomiting, nausea, and ecchymosis. The most common adverse reactions reported with donepezil hydrochloride in controlled clinical trials in patients with mild to moderate Alzheimer’s disease were insomnia, muscle cramp, and fatigue.

Table 2 lists adverse reactions that occurred at an incidence of ≥ 2% in the donepezil hydrochloride group and at a rate greater than placebo in controlled trials in patients with severe Alzheimer’s disease.

Table 2: Adverse reactions with donepezil hydrochloride in patients with severe Alzheimer’s disease
Body System/Adverse Event | Placebo (n = 392) % | Donepezil hydrochloride 10 mg/day (n = 501) %
Percent of Patients with any Adverse Event | 73 | 81
Body as a Whole
Accident | 12 | 13
Infection | 9 | 11
Headache | 3 | 4
Pain | 2 | 3
Back pain | 2 | 3
Fever | 1 | 2
Chest pain | < 1 | 2
Cardiovascular System
Hypertension | 2 | 3
Hemorrhage | 1 | 2
Syncope | 1 | 2
Digestive System
Diarrhea | 4 | 10
Vomiting | 4 | 8
Anorexia | 4 | 8
Nausea | 2 | 6
Hemic and Lymphatic System
Ecchymosis | 2 | 5
Metabolic and Nutritional Systems
Increased creatine phosphokinase | 1 | 3
Dehydration | 1 | 2
Hyperlipemia | < 1 | 2
Nervous System
Insomnia | 4 | 5
Hostility | 2 | 3
Nervousness | 2 | 3
Hallucinations | 1 | 3
Somnolence | 1 | 2
Dizziness | 1 | 2
Depression | 1 | 2
Confusion | 1 | 2
Emotional lability | 1 | 2
Personality disorder | 1 | 2
Skin and Appendages
Eczema | 2 | 3
Urogenital System
Urinary incontinence | 1 | 2

6.2 Postmarketing Experience

The following adverse reactions have been identified during post-approval use of memantine hydrochloride and donepezil hydrochloride. Because these reactions are reported voluntarily from a population of uncertain size, it is not always possible to reliably estimate their frequency or establish a causal relationship to drug exposure.

Memantine Hydrochloride

Acute renal failure, agranulocytosis, cardiac failure congestive, hepatitis, leukopenia (including neutropenia), pancreatitis, pancytopenia, Stevens-Johnson syndrome, suicidal ideation, thrombocytopenia, and thrombotic thrombocytopenic purpura.

Donepezil Hydrochloride

Abdominal pain, agitation, cholecystitis, confusion, convulsions, hallucinations, heart block (all types), hemolytic anemia, hepatitis, hyponatremia, neuroleptic malignant syndrome, pancreatitis, and rash.

7 DRUG INTERACTIONS

7.1 Use of Memantine with Drugs That Make the Urine Alkaline

The clearance of memantine was reduced by about 80% under alkaline urine conditions at pH 8. Therefore, alterations of urine pH towards the alkaline condition may lead to an accumulation of the drug with a possible increase in adverse reactions. Urine pH is altered by diet, drugs (e.g., carbonic anhydrase inhibitors, sodium bicarbonate) and clinical state of the patient (e.g., renal tubular acidosis or severe infections of the urinary tract). Hence, memantine should be used with caution under these conditions.

7.2 Use of Memantine with Other N-methyl-D-aspartate (NMDA) Antagonists

The combined use of memantine hydrochloride with other NMDA antagonists (amantadine, ketamine, and dextromethorphan) has not been systematically evaluated and such use should be approached with caution.

7.3 Effect of Other Drugs on the Metabolism of Donepezil

Inhibitors of CYP3A4 (e.g., ketoconazole) and CYP2D6 (e.g., quinidine), inhibit donepezil metabolism in vitro. Whether there is a clinical effect of quinidine is not known.

Inducers of CYP3A4 (e.g., phenytoin, carbamazepine, dexamethasone, rifampin, and phenobarbital) could increase the rate of elimination of donepezil.

7.4 Use of Donepezil with Anticholinergics

Because of their mechanism of action, cholinesterase inhibitors, including donepezil hydrochloride, have the potential to interfere with the activity of anticholinergic medications.

7.5 Use of Donepezil with Cholinomimetics and Other Cholinesterase Inhibitors

A synergistic effect may be expected when cholinesterase inhibitors, including donepezil hydrochloride, are given concurrently with succinylcholine, similar neuromuscular blocking agents, or cholinergic agonists such as bethanechol.

8. USE IN SPECIFIC POPULATIONS

8.1 Pregnancy

Risk Summary

There are no adequate data on the developmental risk associated with the use of NAMZARIC or its active ingredients (memantine hydrochloride and donepezil hydrochloride) in pregnant women.

Adverse developmental effects (mortality and decreased body weight and skeletal ossification) were observed in the offspring of rats administered memantine or donepezil during pregnancy at doses associated with minimal maternal toxicity. These doses are higher than those used in humans at the recommended daily dose of NAMZARIC [see Data].

In the U.S. general population, the estimated background risk of major birth defects and miscarriage in clinically recognized pregnancies is 2-4% and 15-20%, respectively. The background risk of major birth defects and miscarriage for the indicated population is unknown.

Data

Animal Data

Memantine Hydrochloride

Oral administration of memantine (2, 6, or 18 mg/kg/day) to rats during the period of organogenesis resulted in decreased skeletal ossification in fetuses at the highest dose tested. The higher no-effect dose for adverse developmental effects (6 mg/kg) is 2 times the dose of memantine at the recommended human daily dose (RHD) of NAMZARIC (28 mg memantine/10 mg donepezil) on a body surface area (mg/m^2) basis.

Oral administration of memantine to rabbits (3, 10, or 30 mg/kg/day) during the period of organogenesis resulted in no adverse developmental effects. The highest dose tested is approximately 20 times the dose of memantine at the RHD of NAMZARIC on a mg/m^2 basis.

In rats, memantine (2, 6, or 18 mg/kg/day) was administered orally prior to and throughout mating and, in females, through the period of organogenesis or continuing throughout lactation to weaning. Decreased skeletal ossification in fetuses and decreased body weight in pups were observed at the highest dose tested. The higher no-effect dose for adverse developmental effects (6 mg/kg/day) is 2 times the dose of memantine at the RHD of NAMZARIC on a mg/m^2 basis.

Oral administration of memantine (2, 6, or 18 mg/kg/day) to rats from late gestation throughout lactation to weaning, resulted in decreased pup weights at the highest dose tested. The higher no-effect dose (6 mg/kg/day) is approximately 2 times the dose of memantine at the RHD of NAMZARIC on a mg/m^2 basis.

Donepezil Hydrochloride

Oral administration of donepezil to rats and rabbits during the period of organogenesis resulted in no adverse developmental effects. The highest doses (16 and 10 mg/kg/day, respectively) were approximately 15 and 7 times, respectively, the dose of donepezil at the RHD of NAMZARIC on a mg/m^2 basis.

Oral administration of donepezil (1, 3, or 10 mg/kg/day) to rats during late gestation and throughout lactation to weaning resulted in an increase in stillbirths and offspring mortality at the highest dose tested. The higher no-effect dose (3 mg/kg/day) is approximately 3 times the dose of donepezil at the RHD of NAMZARIC on a mg/m^2 basis.

8.2 Lactation

Risk Summary

There are no data on the presence of memantine or donepezil in human milk, the effects on the breastfed infant, or the effects of NAMZARIC or its metabolites on milk production.

The developmental and health benefits of breastfeeding should be considered along with the mother’s clinical need for NAMZARIC and any potential adverse effects on the breastfed infant from NAMZARIC or from the underlying maternal condition.

8.4 Pediatric Use

Safety and effectiveness of NAMZARIC in pediatric patients have not been established.

Memantine failed to demonstrate efficacy in two 12-week controlled clinical studies of 578 pediatric patients aged 6-12 years with autism spectrum disorders (ASD), including autism, Asperger’s disorder and Pervasive Development Disorder - Not Otherwise Specified (PDD-NOS). Memantine has not been studied in pediatric patients under 6 years of age or over 12 years of age. Memantine treatment was initiated at 3 mg/day and the dose was escalated to the target dose (weight-based) by week 6. Oral doses of memantine 3, 6, 9, or 15 mg extended-release capsules were administered once daily to patients with weights < 20 kg, 20-39 kg, 40-59 kg and ≥ 60 kg, respectively.

In a randomized, 12-week double-blind, placebo-controlled parallel study (Study A) in patients with autism, there was no statistically significant difference in the Social Responsiveness Scale (SRS) total raw score between patients randomized to memantine (n=54) and those randomized to placebo (n=53). In a 12-week responder-enriched randomized withdrawal study (Study B) in 471 patients with ASD, there was no statistically significant difference in the loss of therapeutic response rates between patients randomized to remain on full-dose memantine (n=153) and those randomized to switch to placebo (n=158).

The overall risk profile of memantine in pediatric patients was generally consistent with the known risk profile in adults [see Adverse Reactions (6.1)].

In Study A, the adverse reactions in the memantine group (n=56) that were reported in at least 5% of patients and at least twice the frequency of the placebo group (N=58) are listed in Table 3:

Table 3: Study A Commonly Reported Adverse Reactions With a Frequency ≥ 5% and Twice That of Placebo
Adverse Reaction | Memantine N=56 | Placebo N=58
Cough | 8.9% | 3.4%
Influenza | 7.1% | 3.4%
Rhinorrhea | 5.4% | 0%
Agitation | 5.4% | 1.7%
Discontinuations due to adverse reactionsa
Aggression | 3.6% | 1.7%
Irritability | 1.8% | 3.4%
a Reported adverse reactions leading to discontinuation in more than one patient in either treatment group.

The adverse reactions that were reported in at least 5% of patients in the 12-48 week open-label study to identify responders to enroll in Study B are listed in Table 4:

Table 4: 12-48 Week Open Label Lead-In study to Study B Commonly Reported Adverse Reactions with a Frequency ≥ 5%
Adverse Reaction | Memantine N=903
Headache | 8.0%
Nasopharyngitis | 6.3%
Pyrexia | 5.8%
Irritability | 5.4%
Discontinuations due to adverse reactionsa
Irritability | 1.2%
Aggression | 1.0%
a At least 1% incidence of adverse reactions leading to premature discontinuation.

In the randomized withdrawal study (Study B), the adverse reaction in patients randomized to placebo (n=160) and reported in at least 5% of patients and at twice the frequency of the full-dose memantine treatment group (n=157) was irritability (5.0% vs 2.5%).

In a juvenile animal study, male and female juvenile rats were administered memantine (15, 30, and 45 mg/kg/day) starting on postnatal day (PND) 14 through PND 70. Body weights were reduced at 45 mg/kg/day. Delays in sexual maturation were noted in male and female rats at doses ≥ 30 mg/kg/day. Memantine induced neuronal lesions in several areas of the brain on PND 15 and 17 at doses ≥ 30 mg/kg/day. Behavioral toxicity (decrease percent of auditory startle habituation) was noted for animals in the 45 mg/kg/day dose group. The 15 mg/kg/day dose was considered the No-Observed-Adverse-Effect-Level (NOAEL) for this study.

In a second juvenile rat toxicity study, male and female juvenile rats were administered memantine (1, 3, 8, 15, 30, and 45 mg/kg/day) starting on postnatal day (PND) 7 through PND 70. Due to early memantine-related mortality, the 30 and 45 mg/kg/day dose groups were terminated without further evaluation. Memantine induced apoptosis or neuronal degeneration in several areas of the brain on PND 8, 10, and 17 at a dose of 15 mg/kg/day. The NOAEL for apoptosis and neuronal degeneration was 8 mg/kg/day. Behavioral toxicity (effects on motor activity, auditory startle habituation, and learning and memory) was noted at doses ≥ 3 mg/kg/day during treatment, but was not seen after drug discontinuation. Therefore, the 1 mg/kg/day dose was considered the NOAEL for the neurobehavioral effect in this study.

8.5 Geriatric Use

Memantine Hydrochloride

The majority of people with Alzheimer’s disease are 65 years and older. In the clinical study of memantine hydrochloride extended-release, the mean age of patients was approximately 77 years; over 91% of patients were 65 years of age and older, 67% were 75 years of age and older, and 14% were 85 years of age and older. The efficacy and safety data presented in the clinical trials section were obtained from these patients. There were no clinically meaningful differences in most adverse events reported by patients ≥ 65 years old and < 65 years old.

Donepezil Hydrochloride

The mean age of patients enrolled in the clinical studies with donepezil hydrochloride was 73 years; 80% of these patients were between 65 and 84 years of age, and 49% of patients 75 years of age and older. The efficacy and safety data presented in the clinical trials section were obtained from these patients. There were no clinically significant differences in most adverse events reported by patients ≥ 65 years old and < 65 years old.

8.6 Renal Impairment

A dosage reduction is recommended in patients with severe renal impairment [see Dosage and Administration (2.3) and Clinical Pharmacology (12.3)]. No dosage adjustment is needed in patients with mild or moderate renal impairment.

8.7 Hepatic Impairment

No dosage adjustment is needed in patients with mild or moderate hepatic impairment. NAMZARIC has not been studied in patients with severe hepatic impairment [see Clinical Pharmacology (12.3)].

10 OVERDOSAGE

Memantine hydrochloride and donepezil hydrochloride are the two active ingredients of NAMZARIC. No specific antidote for memantine hydrochloride overdose is known; however, elimination of memantine can be increased by acidification of the urine. Tertiary anticholinergics such as atropine may be used as an antidote for donepezil hydrochloride overdose. In managing cases of overdose, consider the possibility of multiple drug involvement. In case of overdose, call Poison Control Center at 1-800-222-1222 for the latest recommendation. In general, supportive measures should be utilized, and treatment should be symptomatic.

Memantine Hydrochloride

Signs and symptoms most often accompanying overdosage with other formulations of memantine in clinical trials and from worldwide marketing experience, alone or in combination with other drugs and/or alcohol, include agitation, asthenia, bradycardia, confusion, coma, dizziness, ECG changes, increased blood pressure, lethargy, loss of consciousness, psychosis, restlessness, slowed movement, somnolence, stupor, unsteady gait, visual hallucinations, vertigo, vomiting, and weakness. The largest known ingestion of memantine worldwide was 2 grams in an individual who took memantine in conjunction with unspecified antidiabetic medications. This person experienced coma, diplopia, and agitation, but subsequently recovered.

One patient participating in a memantine hydrochloride extended-release clinical trial unintentionally took 112 mg of memantine hydrochloride extended-release daily for 31 days and experienced elevated serum uric acid, elevated serum alkaline phosphatase, and low platelet count.

No fatalities have been noted with overdoses of memantine alone. A fatal outcome has very rarely been reported when memantine has been ingested as part of overdosing with multiple drugs; in those instances, the relationship between memantine and a fatal outcome has been unclear.

Donepezil Hydrochloride

Overdosage with cholinesterase inhibitors can result in cholinergic crisis characterized by severe nausea, vomiting, salivation, sweating, bradycardia, hypotension, respiratory depression, collapse, and convulsions. Increasing muscle weakness is a possibility and may result in death if respiratory muscles are involved. Tertiary anticholinergics such as atropine may be used as an antidote for donepezil hydrochloride overdosage. Intravenous atropine sulfate titrated to effect is recommended: an initial dose of 1.0 to 2.0 mg IV with subsequent doses based upon clinical response. Atypical responses in blood pressure and heart rate have been reported with other cholinomimetics when coadministered with quaternary anticholinergics such as glycopyrrolate. It is not known whether donepezil hydrochloride and/or its metabolites can be removed by dialysis (hemodialysis, peritoneal dialysis, or hemofiltration).

Dose-related signs of toxicity in animals included reduced spontaneous movement, prone position, staggering gait, lacrimation, clonic convulsions, depressed respiration, salivation, miosis, tremors, fasciculation, and lower body surface temperature.

11 DESCRIPTION

NAMZARIC contains memantine, an orally active NMDA receptor antagonist, as the hydrochloride salt and donepezil, a reversible inhibitor of the enzyme acetylcholinesterase, as the hydrochloride salt.

Memantine Hydrochloride

The chemical name for memantine hydrochloride is 1-amino-3,5-dimethyladamantane hydrochloride with the following structural formula:

The molecular formula is C12H21N•HCl and the molecular weight is 215.76. Memantine hydrochloride occurs as a fine white to off-white powder.

Donepezil Hydrochloride

The chemical name for donepezil hydrochloride is 2,3-dihydro-5,6-dimethoxy-2-[[1-(phenylmethyl)-4-piperidinyl]methyl]-1H-inden-1-one hydrochloride.

The molecular formula is C24H29NO3•HCl and the molecular weight is 415.96. Donepezil hydrochloride is a white crystalline powder.

NAMZARIC extended-release capsules contain 7 mg, 14, 21 mg or 28 mg memantine hydrochloride, 10 mg donepezil hydrochloride, and the following inactive ingredients: colloidal silicon dioxide, corn starch, ethylcellulose, hypromellose, lactose monohydrate, magnesium stearate, medium chain triglycerides, microcrystalline cellulose, oleic acid, polyethylene glycol, povidone, sugar spheres, and talc. The capsule shells contain gelatin and titanium dioxide and are imprinted with shellac glaze and black iron oxide. Colorants are FD&C Blue No. 1 (7 mg/10 mg, 14 mg/10 mg, 28 mg/10 mg), FD&C Yellow No. 6 (7 mg/10 mg, 21 mg/10 mg), red iron oxide (7 mg/10 mg, 21 mg/10 mg), and yellow iron oxide (7 mg/10 mg, 14 mg/10 mg, 21 mg/10 mg).

12 CLINICAL PHARMACOLOGY

12.1 Mechanism of Action

NAMZARIC capsules contain two approved medications: memantine hydrochloride and donepezil hydrochloride. Each of those medications is postulated to have a different mechanism in Alzheimer’s disease.

Memantine

Persistent activation of central nervous system NMDA receptors by the excitatory amino acid glutamate has been hypothesized to contribute to the symptomatology of Alzheimer’s disease. Memantine is postulated to exert its therapeutic effect through its action as a low to moderate affinity uncompetitive (open channel) NMDA receptor antagonist which binds preferentially to the NMDA receptor-operated cation channels. There is no evidence that memantine prevents or slows neurodegeneration in patients with Alzheimer’s disease.

Donepezil

Current theories on the pathogenesis of the cognitive signs and symptoms of Alzheimer’s disease attribute some of them to a deficiency of cholinergic neurotransmission. Donepezil is postulated to exert its therapeutic effect by enhancing cholinergic function. This is accomplished by increasing the concentration of acetylcholine in the central nervous system through reversible inhibition of its hydrolysis by acetylcholinesterase. There is no evidence that donepezil prevents or slows neurodegeneration in patients with Alzheimer’s disease.

12.3 Pharmacokinetics

NAMZARIC

NAMZARIC was bioequivalent to co-administration of individual memantine hydrochloride extended-release and donepezil hydrochloride.

Exposure (AUC and Cmax) of memantine and donepezil following NAMZARIC administration in the fed or fasted state was similar. Further, exposure of memantine and donepezil following NAMZARIC administration as intact capsule or capsule contents sprinkled on applesauce was similar in healthy subjects.

Memantine Hydrochloride

Memantine is well absorbed after oral administration and has linear pharmacokinetics over the therapeutic dose range. It is excreted predominantly unchanged in urine and has a terminal elimination half-life of about 60-80 hours. In a study comparing 28 mg once-daily memantine hydrochloride extended-release to 10 mg twice-daily memantine hydrochloride, Cmax and AUC0-24 values were 48% and 33% higher for the memantine hydrochloride extended-release dosage regimen, respectively.

Absorption

After multiple dose administration of memantine hydrochloride extended-release, memantine peak concentrations occur around 9-12 hours postdose. There is no difference in the absorption of memantine hydrochloride extended-release when the capsule is taken intact or when the contents are sprinkled on applesauce.

After single-dose administration, there is no difference in memantine exposure, based on Cmax or AUC, for memantine hydrochloride extended-release when the drug product is administered with food or on an empty stomach. However, peak plasma concentrations are achieved about 18 hours after administration with food versus approximately 25 hours after administration on an empty stomach.

Distribution

The mean volume of distribution of memantine is 9-11 L/kg and the plasma protein binding is low (45%).

Metabolism

Memantine undergoes partial hepatic metabolism. The hepatic microsomal CYP450 enzyme system does not play a significant role in the metabolism of memantine.

Elimination

Memantine is excreted predominantly in the urine, unchanged, and has a terminal elimination half-life of about 60-80 hours. About 48% of administered drug is excreted unchanged in urine; the remainder is converted primarily to three polar metabolites which possess minimal NMDA receptor antagonistic activity: the N-glucuronide conjugate, 6-hydroxy memantine, and 1-nitroso-deaminated memantine. A total of 74% of the administered dose is excreted as the sum of the parent drug and the N-glucuronide conjugate. Renal clearance involves active tubular secretion moderated by pH dependent tubular reabsorption.

Pharmacokinetics in Special Populations

Renal Impairment

Memantine pharmacokinetics were evaluated following single oral administration of 20 mg memantine hydrochloride in 8 subjects with mild renal impairment (creatinine clearance, CLcr, > 50 – 80 mL/min), 8 subjects with moderate renal impairment (CLcr 30 – 49 mL/min), 7 subjects with severe renal impairment (CLcr 5 – 29 mL/min) and 8 healthy subjects (CLcr > 80 mL/min) matched as closely as possible by age, weight and gender to the subjects with renal impairment. Mean AUC0-∞ increased by 4%, 60%, and 115% in subjects with mild, moderate, and severe renal impairment, respectively, compared to healthy subjects. The terminal elimination half-life increased by 18%, 41%, and 95% in subjects with mild, moderate, and severe renal impairment, respectively, compared to healthy subjects [see Dosage and Administration (2.3) and Use in Specific Populations (8.6)].

Hepatic Impairment

Memantine pharmacokinetics were evaluated following the administration of single oral doses of 20 mg in 8 subjects with moderate hepatic impairment (Child-Pugh Class B, score 7-9) and 8 subjects who were age-, gender-, and weight-matched to the hepatically-impaired subjects.

There was no change in memantine exposure (based on Cmax and AUC) in subjects with moderate hepatic impairment as compared with healthy subjects. However, terminal elimination half-life increased by about 16% in subjects with moderate hepatic impairment as compared with healthy subjects. The pharmacokinetics of memantine has not been evaluated in patients with severe hepatic impairment.

Gender

Following multiple dose administration of memantine hydrochloride 20 mg daily, females had about 45% higher exposure than males, but there was no difference in exposure when body weight was taken into account.

Elderly

The pharmacokinetics of memantine in young and elderly subjects are similar.

Drug-Drug Interactions

Use with Cholinesterase Inhibitors

Coadministration of memantine with the AChE inhibitor donepezil hydrochloride did not affect the pharmacokinetics of either compound. Furthermore, memantine did not affect AChE inhibition by donepezil. In a 24-week controlled clinical study in patients with moderate to severe Alzheimer’s disease, the adverse event profile observed with a combination of memantine immediate-release and donepezil was similar to that of donepezil alone.

Effect of Memantine on the Metabolism of Other Drugs

In vitro studies conducted with marker substrates of CYP450 enzymes (CYP1A2, -2A6, -2C9, -2D6, -2E1, -3A4) showed minimal inhibition of these enzymes by memantine. In addition, in vitro studies indicate that at concentrations exceeding those associated with efficacy, memantine does not induce the cytochrome P450 isozymes CYP1A2, -2C9, -2E1 and -3A4/5. No pharmacokinetic interactions with drugs metabolized by these enzymes are expected.

Pharmacokinetic studies evaluated the potential of memantine for interaction with warfarin and bupropion. Memantine did not affect the pharmacokinetics of the CYP2B6 substrate bupropion or its metabolite hydroxybupropion. Furthermore, memantine did not affect the pharmacokinetics or pharmacodynamics of warfarin as assessed by prothrombin INR.

Effect of Other Drugs on Memantine

Memantine is predominantly renally eliminated, and drugs that are substrates and/or inhibitors of the CYP450 system are not expected to alter the pharmacokinetics of memantine. A single dose of bupropion did not affect the pharmacokinetics of memantine at steady state.

Drugs Eliminated via Renal Mechanisms

Because memantine is eliminated in part by tubular secretion, coadministration of drugs that use the same renal cationic system, including hydrochlorothiazide (HCTZ), triamterene (TA), metformin, cimetidine, ranitidine, quinidine, and nicotine, could potentially result in altered plasma levels of both agents. However, coadministration of memantine hydrochloride and HCTZ/TA did not affect the bioavailability of either memantine or TA, and the bioavailability of HCTZ decreased by 20%. In addition, coadministration of memantine hydrochloride with the antihyperglycemic drug Glucovance® (glyburide and metformin hydrochloride) did not affect the pharmacokinetics of memantine, metformin, and glyburide. Furthermore, memantine did not modify the serum glucose lowering effect of Glucovance®, indicating the absence of a pharmacodynamic interaction.

Drugs Highly Bound to Plasma Proteins

Because the plasma protein binding of memantine is low (45%), an interaction with drugs that are highly bound to plasma proteins, such as warfarin and digoxin, is unlikely.

Donepezil Hydrochloride

Pharmacokinetics of donepezil are linear over a dose range of 1-10 mg given once daily. The rate and extent of absorption of donepezil hydrochloride tablets are not influenced by food.

Donepezil is absorbed with a relative oral bioavailability of 100% and reaches peak plasma concentrations in 3 to 4 hours.

The elimination half-life of donepezil is about 70 hours, and the mean apparent plasma clearance (Cl/F) is 0.13 – 0.19 L/hr/kg. Following multiple dose administration, donepezil accumulates in plasma by 4-7 fold, and steady state is reached within 15 days. The steady-state volume of distribution is 12 - 16 L/kg. Donepezil is approximately 96% bound to human plasma proteins, mainly to albumins (about 75%) and alpha-1-acid glycoprotein (about 21%) over the concentration range of 2-1000 ng/mL.

Donepezil is both excreted in the urine intact and extensively metabolized to four major metabolites, two of which are known to be active, and a number of minor metabolites, not all of which have been identified. Donepezil is metabolized by CYP 450 isoenzymes 2D6 and 3A4 and undergoes glucuronidation. Following administration of ^14C-labeled donepezil, plasma radioactivity, expressed as a percent of the administered dose, was present primarily as intact donepezil (53%) and as 6-O-desmethyl donepezil (11%), which has been reported to inhibit AChE to the same extent as donepezil in vitro and was found in plasma at concentrations equal to about 20% of donepezil. Approximately 57% and 15% of the total radioactivity was recovered in urine and feces, respectively, over a period of 10 days, while 28% remained unrecovered, with about 17% of the donepezil dose recovered in the urine as unchanged drug. Examination of the effect of CYP2D6 genotype in Alzheimer’s patients showed differences in clearance values among CYP2D6 genotype subgroups. When compared to the extensive metabolizers, poor metabolizers had a 31.5% slower clearance and ultra-rapid metabolizers had a 24% faster clearance. These results suggest CYP2D6 has a minor role in the metabolism of donepezil.

Renal Impairment

In a study of 11 patients with moderate to severe renal impairment (CLcr < 18 mL/min/ 1.73 m^2) the clearance of donepezil hydrochloride did not differ from 11 age- and sex-matched healthy subjects.

Hepatic Disease

In a study of 10 patients with stable alcoholic cirrhosis, the clearance of donepezil hydrochloride was decreased by 20% relative to 10 healthy age- and sex-matched subjects.

Age

No formal pharmacokinetic study was conducted to examine age-related differences in the pharmacokinetics of donepezil hydrochloride. Population pharmacokinetic analysis suggested that the clearance of donepezil in patients decreases with increasing age. When compared with 65-year old, subjects, 90-year old subjects have a 17% decrease in clearance, while 40-year old subjects have a 33% increase in clearance. The effect of age on donepezil clearance may not be clinically significant.

Gender and Race

No specific pharmacokinetic study was conducted to investigate the effects of gender and race on the disposition of donepezil hydrochloride. However, retrospective pharmacokinetic analysis and population pharmacokinetic analysis of plasma donepezil concentrations measured in patients with Alzheimer’s disease indicate that gender and race (Japanese and Caucasians) did not affect the clearance of donepezil hydrochloride to an important degree.

Body weight

There was a relationship noted between body weight and clearance. Over the range of body weight from 50 kg to 110 kg, clearance increased from 7.77 L/h to 14.04 L/h, with a value of 10 L/h for 70 kg individuals.

Drug-Drug Interactions

Effect of Donepezil hydrochloride on the Metabolism of Other Drugs

No in vivo clinical trials have investigated the effect of donepezil hydrochloride on the clearance of drugs metabolized by CYP3A4 (e.g., cisapride, terfenadine) or by CYP2D6 (e.g., imipramine). However, in vitro studies show a low rate of binding to these enzymes (mean Ki about 50-130 µM), that, given the therapeutic plasma concentrations of donepezil (164 nM), indicates little likelihood of interference. Based on in vitro studies, donepezil shows little or no evidence of direct inhibition of CYP2B6, CYP2C8, and CYP2C19 at clinically relevant concentrations.

Whether donepezil hydrochloride has any potential for enzyme induction is not known. Formal pharmacokinetic studies evaluated the potential of donepezil hydrochloride for interaction with theophylline, cimetidine, warfarin, digoxin, and ketoconazole. No effects of donepezil hydrochloride on the pharmacokinetics of these drugs were observed.

Effect of Other Drugs on the Metabolism of Donepezil hydrochloride

A small effect of CYP2D6 inhibitors was identified in a population pharmacokinetic analysis of plasma donepezil concentrations measured in patients with Alzheimer’s disease. Donepezil clearance was reduced by approximately 17% in patients taking 10 or 23 mg in combination with a known CYP2D6 inhibitor. This result is consistent with the conclusion that CYP2D6 is a minor metabolic pathway of donepezil.

Formal pharmacokinetic studies demonstrated that the metabolism of donepezil hydrochloride is not significantly affected by concurrent administration of digoxin or cimetidine.

An in vitro study showed that donepezil was not a substrate of P-glycoprotein.

Drugs Highly Bound to Plasma Proteins

Drug displacement studies have been performed in vitro between this highly bound drug (96%) and other drugs such as furosemide, digoxin, and warfarin. Donepezil hydrochloride at concentrations of 0.3-10 micrograms/mL did not affect the binding of furosemide (5 micrograms/mL), digoxin (2 ng/mL), and warfarin (3 micrograms/mL) to human albumin. Similarly, the binding of donepezil hydrochloride to human albumin was not affected by furosemide, digoxin, and warfarin.

13 NONCLINICAL TOXICOLOGY

13.1 Carcinogenesis, Mutagenesis, Impairment of Fertility

Memantine

There was no evidence of carcinogenicity in a 113-week oral study in mice at doses up to 40 mg/kg/day (7 times the dose of memantine at the maximum recommended human dose [MRHD] of NAMZARIC [28 mg/10 mg] on a mg/m^2 basis). There was also no evidence of carcinogenicity in rats orally dosed at up to 40 mg/kg/day for 71 weeks followed by 20 mg/kg/day (14 and 7 times the MRHD on a mg/m^2 basis, respectively) through 128 weeks.

Memantine produced no evidence of genotoxic potential when evaluated in the in vitro S. typhimurium or E. coli reverse mutation assay, an in vitro chromosomal aberration test in human lymphocytes, an in vivo cytogenetics assay for chromosome damage in rats, and the in vivo mouse micronucleus assay. The results were equivocal in an in vitro gene mutation assay using Chinese hamster V79 cells.

No impairment of fertility or reproductive performance was seen in rats administered up to 18 mg/kg/day (6 times the dose of memantine at the MRHD of NAMZARIC on a mg/m^2 basis) orally from 14 days prior to mating through gestation and lactation in females, or for 60 days prior to mating in males.

Donepezil

No evidence of carcinogenic potential was obtained in an 88-week carcinogenicity study of donepezil conducted in mice at oral doses up to 180 mg/kg/day (approximately 90 times the dose of donepezil at the MRHD of NAMZARIC on a mg/m^2 basis), or in a 104-week carcinogenicity study in rats at oral doses up to 30 mg/kg/day (approximately 30 times the dose of donepezil at the MRHD of NAMZARIC on a mg/m^2 basis).

Donepezil was negative in a battery of genotoxicity assays (in vitro bacterial reverse mutation, in vitro mouse lymphoma tk, in vitro chromosomal aberration, and in vivo mouse micronucleus).

Donepezil had no effect on fertility in rats at oral doses up to 10 mg/kg/day (approximately 10 times the dose of donepezil at the MRHD of NAMZARIC on a mg/m^2 basis) when administered to males and females prior to and during mating and continuing in females through implantation.

13.2 Animal Toxicology and/or Pharmacology

Memantine induced neuronal lesions (vacuolation and necrosis) in the multipolar and pyramidal cells in cortical layers III and IV of the posterior cingulate and retrosplenial neocortices in rats, similar to those which are known to occur in rodents administered other NMDA receptor antagonists. Lesions were seen after a single dose of memantine. In a study in which rats were given daily oral doses of memantine for 14 days, the no-effect dose for neuronal necrosis was 4 times the dose of memantine at the MRHD of NAMZARIC on a mg/m^2 basis.

In acute and repeat-dose neurotoxicity studies in female rats, oral administration of memantine and donepezil in combination resulted in increased incidence, severity, and distribution of neurodegeneration compared with memantine alone. The no-effect levels of the combination were associated with clinically relevant plasma memantine and donepezil exposures.

The relevance of these findings to humans is unknown.

14 CLINICAL STUDIES

The effectiveness of NAMZARIC as a treatment for patients with moderate to severe Alzheimer’s disease was established by demonstrating the bioequivalence of NAMZARIC with co-administered memantine hydrochloride extended-release and donepezil hydrochloride [see Clinical Pharmacology (12.3)].

Memantine Hydrochloride

The effectiveness of memantine hydrochloride extended-release as a treatment for patients with moderate to severe Alzheimer’s disease when coadministered with acetylcholinesterase inhibitors, including donepezil hydrochloride, was based on the results of a double-blind, placebo-controlled trial.

24-week Study of Memantine Hydrochloride Extended-Release

This was a randomized, double-blind clinical investigation in 677 outpatients with moderate to severe Alzheimer’s disease (diagnosed by DSM-IV criteria and NINCDS-ADRDA criteria for AD with a Mini Mental State Examination [MMSE] score ≥ 3 and ≤ 14 at Screening and Baseline) receiving acetylcholinesterase inhibitor (AChEI) therapy at a stable dose for 3 months prior to screening. Approximately 68% of the patients received donepezil as the AChEI. The mean age of patients participating in this trial was 76.5 years, with a range of 49-97 years.

Approximately 72% of patients were female and 94% were Caucasian.

Study Outcome Measures

The effectiveness of memantine hydrochloride extended-release was evaluated in this study using the co-primary efficacy parameters of Severe Impairment Battery (SIB) and the Clinician’s Interview-Based Impression of Change (CIBIC-Plus).

The ability of memantine hydrochloride extended-release to improve cognitive performance was assessed with the Severe Impairment Battery (SIB), a multi-item instrument that has been validated for the evaluation of cognitive function in patients with moderate to severe dementia. The SIB examines selected aspects of cognitive performance, including elements of attention, orientation, language, memory, visuospatial ability, construction, praxis, and social interaction. The SIB scoring range is from 0 to 100, with lower scores indicating greater cognitive impairment.

The ability of memantine hydrochloride extended-release to produce an overall clinical effect was assessed using a Clinician’s Interview Based Impression of Change that required the use of caregiver information, the CIBIC-Plus. The CIBIC-Plus is not a single instrument and is not a standardized instrument like the ADCS-ADL or SIB. Clinical trials for investigational drugs have used a variety of CIBIC formats, each different in terms of depth and structure. As such, results from a CIBIC-Plus reflect clinical experience from the trial or trials in which it was used and cannot be compared directly with the results of CIBIC-Plus evaluations from other clinical trials. The CIBIC-Plus used in this trial was a structured instrument based on a comprehensive evaluation at baseline and subsequent time points of four domains: general (overall clinical status), functional (including activities of daily living), cognitive, and behavioral. It represents the assessment of a skilled clinician using validated scales based on his/her observation during an interview with the patient, in combination with information supplied by a caregiver familiar with the behavior of the patient over the interval rated. The CIBIC-Plus is scored as a seven point categorical rating, ranging from a score of 1, indicating “marked improvement” to a score of 4, indicating “no change” to a score of 7, indicating “marked worsening.” The CIBIC-Plus has not been systematically compared directly to assessments not using information from caregivers (CIBIC) or other global methods.

Study Results

In this study, 677 patients were randomized to one of the following 2 treatments: memantine hydrochloride extended-release 28 mg/day or placebo, while still receiving an AChEI (either donepezil, galantamine, or rivastigmine).

Effects on Severe Impairment Battery (SIB)

Figure 1 shows the time course for the change from baseline in SIB score for the two treatment groups completing the 24 weeks of the study. At 24 weeks of treatment, the mean difference in the SIB change scores for the memantine hydrochloride extended-release 28 mg/AChEI-treated (combination therapy) patients compared to the patients on placebo/AChEI (monotherapy) was 2.6 units. Using an LOCF analysis, memantine hydrochloride extended-release 28 mg/AChEI treatment was statistically significantly superior to placebo/AChEI.

Figure 1: Time course of the change from baseline in SIB score for patients completing 24 weeks of treatment.

Figure 2 shows the cumulative percentages of patients from each treatment group who had attained at least the measure of improvement in SIB score shown on the X-axis. The curves show that both patients assigned to memantine hydrochloride extended-release 28 mg/AChEI and placebo/AChEI have a wide range of responses, but that the memantine hydrochloride extended-release 28 mg/AChEI group is more likely to show an improvement or a smaller decline.

Figure 2: Cumulative percentage of patients completing 24 weeks of double-blind treatment with specified changes from baseline in SIB scores.

Effects on Severe Impairment Battery (SIB) in the Subset of Patients on Concomitant Donepezil Therapy

Approximately 68% of the patients randomized to receive either memantine hydrochloride extended-release 28 mg or placebo were taking donepezil at Baseline and throughout the study. At 24 weeks of treatment, in patients on concomitant donepezil treatment, the mean difference in the SIB change scores for the memantine hydrochloride extended-release 28 mg-treated patients compared to patients on placebo (2.7 units) was similar to that observed for the entire study population (2.6 units).

Effects of Clinician's Interview-Based Impression of Change Plus Caregiver Input (CIBIC-Plus)

Figure 3 shows the time course for the CIBIC-Plus score for patients in the two treatment groups completing the 24 weeks of the study. At 24 weeks of treatment, the mean difference in the CIBIC-Plus scores for the memantine hydrochloride extended-release 28 mg/AChEI-treated patients compared to the patients on placebo/AChEI was 0.3 units. Using an LOCF analysis, memantine hydrochloride extended-release 28 mg/AChEI treatment was statistically significantly superior to placebo/AChEI.

Figure 3: Time course of the CIBIC-Plus score for patients completing 24 weeks of treatment.

Figure 4 is a histogram of the percentage distribution of CIBIC-Plus scores attained by patients assigned to each of the treatment groups who completed 24 weeks of treatment.

Figure 4: Distribution of CIBIC-Plus ratings at week 24.

Effects on CIBIC-Plus in the Subset of Patients on Concomitant Donepezil Therapy

Approximately 68% of the patients randomized to receive either memantine hydrochloride extended-release 28 mg or placebo were taking donepezil at baseline and throughout the study. At 24 weeks of treatment, in patients on concomitant donepezil, the mean difference in the CIBIC-Plus scores for the memantine hydrochloride extended-release 28 mg-treated patients compared to patients on placebo (0.3 units) was similar to that observed for the entire study population (0.3 units).

Donepezil Hydrochloride

The effectiveness of donepezil hydrochloride as a treatment for patients with severe Alzheimer’s disease was based on the results of two double-blind, placebo-controlled trials.

6-Month Study of Donepezil Hydrochloride

This was a randomized, double-blind, placebo-controlled clinical study conducted in Sweden in patients with probable or possible Alzheimer's disease diagnosed by NINCDS-ADRDA and DSM-IV criteria, MMSE: range of 1-10. Two hundred and forty eight (248) patients with severe Alzheimer's disease were randomized to donepezil hydrochloride or placebo. For patients randomized to donepezil hydrochloride, treatment was initiated at 5 mg once daily for 28 days and then increased to 10 mg once daily. At the end of the 6 month treatment period, 90.5% of the donepezil hydrochloride treated patients were receiving the 10 mg/day dose. The mean age of patients was 84.9 years, with a range of 59 to 99. Approximately 77% of patients were women, and 23% were men. Almost all patients were Caucasian. Probable AD was diagnosed in the majority of the patients (83.6% of donepezil hydrochloride treated patients and 84.2% of placebo treated patients).

Study Outcome Measures

The effectiveness of treatment with donepezil hydrochloride was evaluated using a dual outcome assessment strategy that evaluated cognitive function using an instrument designed for more impaired patients and overall function through caregiver-rated assessment. This study showed that patients on donepezil hydrochloride experienced significant improvement on both measures compared to placebo.

The ability of donepezil hydrochloride to improve cognitive performance was assessed with the SIB.

Daily function was assessed using the Modified Alzheimer's Disease Cooperative Study Activities of Daily Living Inventory for Severe Alzheimer's Disease (ADCS-ADL-severe). The ADCS-ADL-severe is derived from the Alzheimer's Disease Cooperative Study Activities of Daily Living Inventory, which is a comprehensive battery of ADL questions used to measure the functional capabilities of patients. Each ADL item is rated from the highest level of independent performance to complete loss. The ADCS-ADL-severe is a subset of 19 items, including ratings of the patient's ability to eat, dress, bathe, use the telephone, get around (or travel), and perform other activities of daily living; it has been validated for the assessment of patients with moderate to severe dementia. The ADCS-ADL-severe has a scoring range of 0 to 54, with the lower scores indicating greater functional impairment. The investigator performs the inventory by interviewing a caregiver, in this study a nurse staff member, familiar with the functioning of the patient.

Effects on the SIB

Figure 5 shows the time course for the change from baseline in SIB score for the two treatment groups over the 6 months of the study. At 6 months of treatment, the mean difference in the SIB change scores for donepezil hydrochloride treated patients compared to patients on placebo was 5.9 points. Donepezil hydrochloride treatment was statistically significantly superior to placebo.

Figure 5. Time Course of the Change from Baseline in SIB Score for Patients Completing 6 months of Treatment.

Figure 6 illustrates the cumulative percentages of patients from each of the two treatment groups who attained the measure of improvement in SIB score shown on the X-axis. While patients assigned both to donepezil hydrochloride and to placebo have a wide range of responses, the curves show that the donepezil hydrochloride group is more likely to show a greater improvement in cognitive performance.

Figure 6. Cumulative Percentage of Patients Completing 6 Months of Double-blind Treatment with Particular Changes from Baseline in SIB Scores.

Figure 7. Time Course of the Change from Baseline in ADCS-ADL-Severe Score for Patients Completing 6 Months of Treatment.

Effects on the ADCS-ADL-severe

Figure 7 illustrates the time course for the change from baseline in ADCS-ADL-severe scores for patients in the two treatment groups over the 6 months of the study. After 6 months of treatment, the mean difference in the ADCS-ADL-severe change scores for donepezil hydrochloride treated patients compared to patients on placebo was 1.8 points. Donepezil hydrochloride treatment was statistically significantly superior to placebo.

Figure 8 shows the cumulative percentages of patients from each treatment group with specified changes from baseline ADCS-ADL-severe scores. While both patients assigned to donepezil hydrochloride and placebo have a wide range of responses, the curves demonstrate that the donepezil hydrochloride group is more likely to show a smaller decline or an improvement.

Figure 8. Cumulative Percentage of Patients Completing 6 Months of Double-blind Treatment with Particular Changes from Baseline in ADCS-ADL-Severe Scores.

24-Week Study of Donepezil Hydrochloride

In a randomized, double-blind, placebo-controlled study conducted in Japan, 325 patients with severe Alzheimer's disease received doses of 5 mg/day or 10 mg/day of donepezil hydrochloride, administered once daily, or placebo. Patients randomized to treatment with donepezil hydrochloride were to achieve their assigned doses by titration, beginning at 3 mg/day, and extending over a maximum of 6 weeks. Two hundred and forty eight (248) patients completed the study, with similar proportions of patients completing the study in each treatment group. The primary efficacy measures for this study were the SIB and CIBIC-plus.

At 24 weeks of treatment, statistically significant treatment differences were observed between the 10 mg/day dose of donepezil hydrochloride and placebo on both the SIB and CIBIC-plus. The 5 mg/day dose of donepezil hydrochloride showed a statistically significant superiority to placebo on the SIB, but not on the CIBIC-plus.

16 HOW SUPPLIED/STORAGE AND HANDLING

16.1 How Supplied

7 mg memantine hydrochloride and 10 mg donepezil hydrochloride: light green opaque body and an orange opaque cap with a black “FL 7/10” radial imprint.

Bottle of 30: NDC# 0456-1207-30

14 mg memantine hydrochloride and 10 mg donepezil hydrochloride: light green opaque capsules with a black “FL 14/10” radial imprint.
Bottle of 30: NDC# 0456-1214-30
Bottle of 90: NDC# 0456-1214-90
Unit Dose carton (10x10): NDC# 0456-1214-63
Unit Dose blister (10): NDC# 0456-1214-11

21 mg memantine hydrochloride and 10 mg donepezil hydrochloride: white opaque body and an orange opaque cap with a black “FL 21/10” radial imprint.
Bottle of 30: NDC# 0456-1221-30

28 mg memantine hydrochloride and 10 mg donepezil hydrochloride: blue opaque capsules with a black “FL 28/10” radial imprint.
Bottle of 30: NDC# 0456-1228-30
Bottle of 90: NDC# 0456-1228-90
Unit Dose carton (10x10): NDC# 0456-1228-63
Unit Dose blister (10): NDC# 0456-1228-11

Titration Pack NDC# 0456-1229-29
Contains 28 capsules (7 x 7mg/10 mg, 7 x 14 mg/10 mg, 7 x 21 mg/10 mg, 7 x 28 mg/10 mg)

16.2 Storage and Handling

Store at 20°C to 25°C (68°F to 77°F); excursions permitted between 15°C and 30°C (59°F and 86°F) [see USP Controlled Room Temperature]. Dispense in a tight, light-resistant container, as defined in the USP.

17 PATIENT COUNSELING INFORMATION

Advise the patient to read the FDA-approved patient labeling (Patient Information).

Dosing Information

- Instruct patients and caregivers to take NAMZARIC only once daily in the evening, as prescribed [see Dosage and Administration (2.1)].
- If a patient misses a single dose of NAMZARIC, that patient should not double up on the next dose. The next dose should be taken as scheduled [see Dosage and Administration (2.1)].
- Instruct patients and caregivers that NAMZARIC capsules should be swallowed whole. Alternatively, NAMZARIC capsules may be opened and sprinkled on applesauce and the entire contents should be consumed. The capsules should not be divided, chewed, or crushed. Warn patients and caregivers not to use any capsules of NAMZARIC that are damaged or show signs of tampering [see Dosage and Administration (2.2)].

Common Adverse Reactions

Advise patients and caregivers that NAMZARIC may cause headache, diarrhea, dizziness, anorexia, vomiting, nausea, and ecchymosis [see Adverse Reactions (6.1)].

Distributed by:
AbbVie Inc.,
North Chicago, IL 60064

Licensed from Merz Pharma GmbH & Co. KGaA and Adamas Pharmaceuticals, Inc.

NAMZARIC is a trademark of Merz Pharma GmbH & Co. KGaA.

© 2024 AbbVie Inc. All rights reserved.

PATIENT INFORMATION
NAMZARIC® [nam-ZAIR-ick]
(memantine and donepezil hydrochlorides) extended release capsules

What is NAMZARIC?

- NAMZARIC is a prescription medicine used to treat moderate to severe dementia in people with Alzheimer’s disease. NAMZARIC contains 2 medicines, memantine hydrochloride (HCl), an NMDA receptor antagonist, and donepezil HCl, an acetylcholinesterase inhibitor. NAMZARIC is for people who are taking donepezil HCl 10 mg.
- It is not known if NAMZARIC is safe and effective in children.

Do not take NAMZARIC if you have an allergy to memantine HCl, donepezil HCl, medicines that contains piperidines, or any of the ingredients in NAMZARIC. See the end of this leaflet for a complete list of ingredients in NAMZARIC.

Before taking NAMZARIC, tell your doctor about all of your medical conditions, including if you:

- have heart problems including an irregular, slow, or fast heartbeat.
- have asthma or lung problems.
- have seizures.
- have stomach ulcers.
- have bladder or kidney problems.
- have liver problems.
- have surgical, dental, or other medical procedures scheduled and anesthesia may be used.
- are pregnant or plan to become pregnant. It is not known if NAMZARIC can harm an unborn baby.
- are breast-feeding or plan to breastfeed. It is not known if NAMZARIC passes into breast milk. Talk to your doctor about the best way to feed your baby if you take NAMZARIC.

Tell your doctor about all the medicines you take, including prescription and over-the-counter medicines, vitamins, and herbal supplements.

How should I take NAMZARIC?

- Take NAMZARIC exactly as your doctor tells you to take it.
- Do not change your dose or stop taking NAMZARIC without talking to your doctor.
- Take NAMZARIC by mouth 1 time each evening before going to bed.
- Take NAMZARIC with or without food.
- NAMZARIC capsules may be opened and sprinkled on applesauce before swallowing. Sprinkle all of the medicine in the capsule on the applesauce. Do not divide the dose.
- If you do not open and sprinkle NAMZARIC capsules on applesauce, the NAMZARIC capsules must be swallowed whole. Do not divide, chew, or crush NAMZARIC capsules.
- If you miss a dose take NAMZARIC at your next scheduled dose. Do not take 2 doses of NAMZARIC at the same time.
- Do not use any NAMZARIC capsules that are damaged or show signs of tampering.
- If you take too much NAMZARIC, call Poison control center at 1-800-222-1222, or go to the nearest hospital emergency room right away.

What are the possible side effects of NAMZARIC? NAMZARIC may cause serious side effects, including:

- muscle problems if you need anesthesia
- slow heartbeat and fainting. This happens more often in people with heart problems. Call the doctor right away if the patient faints while taking NAMZARIC.
- more stomach acid. This raises the chance of ulcers and bleeding especially when taking NAMZARIC. The risk is higher for patients who had ulcers, or take aspirin or other NSAIDs.
- nausea and vomiting
- difficulty passing urine
- seizures
- worsening of lung problems in people with asthma or other lung disease.

The most common side effects of memantine HCl include:
• headache • diarrhea • dizziness
The most common side effects of donepezil HCl include:
• diarrhea • not wanting to eat (anorexia) • bruising
These are not all the possible side effects of NAMZARIC.
Call your doctor for medical advice about side effects. You may report side effects to FDA at 1-800-FDA-1088.

How should I store NAMZARIC?

Store NAMZARIC at room temperature, about 68°F to 77°F (20°C to 25°C). Capsules should be stored in the original prescription container or other light resistant container.

General information about the safe and effective use of NAMZARIC.
Medicines are sometimes prescribed for purposes other than those listed in a Patient Information leaflet. Do not use NAMZARIC for a condition for which it was not prescribed. Do not give NAMZARIC to other people, even if they have the same symptoms that you have. It may harm them. You can ask your pharmacist or doctor for information about NAMZARIC that is written for health professionals.

What are the ingredients in NAMZARIC?
Active ingredient: memantine hydrochloride and donepezil hydrochloride
Inactive ingredients: colloidal silicon dioxide, corn starch, ethylcellulose, hypromellose, lactose monohydrate, magnesium stearate, medium chain triglycerides, microcrystalline cellulose, oleic acid, polyethylene glycol, povidone, sugar spheres, and talc. The capsule shells contain gelatin and titanium dioxide and are imprinted with shellac glaze and black iron oxide. Colorants are FD&C Blue No. 1 (7 mg/10 mg, 14 mg/10 mg, 28 mg/10 mg) FD&C Yellow No. 6 (7 mg/10 mg, 21 mg/10 mg), red iron oxide (7 mg/10 mg, 21 mg/10 mg) and yellow iron oxide (7 mg/10 mg, 14 mg/10 mg, 21 mg/10 mg).
Distributed by: AbbVie Inc., North Chicago, IL 60064
Licensed from Merz Pharma GmbH & Co. KGaA and Adamas Pharmaceuticals, Inc.
NAMZARIC is a trademark of Merz Pharma GmbH & Co. KGaA-.
© 2024 AbbVie Inc. All rights reserved.

This Patient Information has been approved by the U.S. Food and Drug Administration Revised: 05/2024

PACKAGE LABEL

Principal Display Panel

NDC 0456-1207-30
Rx Only
30 capsules
Namzaric®
(memantine and donepezil
hydrochlorides) extended-
release capsules
7 mg/10 mg per capsule
abbvie

PACKAGE LABEL

Principal Display Panel

NDC 0456-1214-30
Rx only
30 capsules
Namzaric®
(memantine and donepezil
hydrochlorides) extended-
release capsules
14 mg/10 mg per capsule
abbvie

PACKAGE LABEL

Principal Display Panel

NDC 0456-1221-30
Rx only
30 capsules
Namzaric®
(memantine and donepezil
hydrochlorides) extended-
release capsules
21 mg/10 mg per capsule
abbvie

PACKAGE LABEL

Principal Display Panel

NDC 0456-1228-30
Rx only
30 capsules
Namzaric®
(memantine and donepezil
hydrochlorides) extended-
release capsules
28 mg/10 mg per capsule
abbvie

PACKAGE LABEL

Principal Display Panel

Titration Pack
NDC 0456-1229-29
Namzaric®
(memantine and donepezil hydrochlorides)
extended-release capsules

Week 1 7mg/10 mg
Week 2 14mg/10 mg
Week 3 21mg/10 mg
Week 4 28mg/10 mg

This Titration Pack includes:
NAMZARIC® extended release capsules
for your first 4 weeks of therapy.
For detailed dosing instructions, see inside panel.
This Titration Pack is not to be refilled.